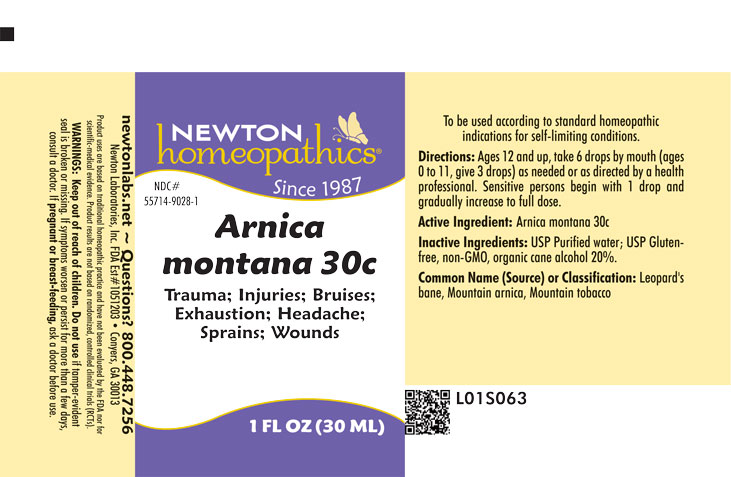 DRUG LABEL: Arnica montana
NDC: 55714-9028 | Form: LIQUID
Manufacturer: Newton Laboratories, Inc.
Category: homeopathic | Type: HUMAN OTC DRUG LABEL
Date: 20260128

ACTIVE INGREDIENTS: ARNICA MONTANA 30 [hp_C]/1 mL
INACTIVE INGREDIENTS: WATER; ALCOHOL

Arnica 9028L

INDICATIONS & USAGE SECTION

Trauma; Injuries; Bruises; Exhaustion; Headache; Sprains; Wounds

DOSAGE & ADMINISTRATION SECTION

Directions: Ages 12 and up, take 6 drops by mouth, (ages 0 to 11, give 3 drops) as needed or as directed by a health professional. Sensitive persons begin with 1 drop and gradually increase to full dose.

OTC - ACTIVE INGREDIENT SECTION

Arnica montana 30c.

OTC - PURPOSE SECTION

Trauma; Injuries; Bruises; Exhaustion; Headache; Sprains; Wounds

INACTIVE INGREDIENT SECTION

Inactive Ingredients: USP Purified Water; USP Gluten-free, non-GMO, organic cane alcohol 20%.

QUESTIONS SECTION

newtonlabs.net – Questions? 800.448.7256

Newton Laboratories, Inc. FDA Est # 1051203 - Conyers, GA 30013

WARNINGS SECTION

Warning: Keep out of reach of children. Do not use if tamper - evident seal is broken or missing. If symptoms worsen or persist for more than a few days, consult a doctor. If pregnant or breast-feeding, ask a doctor before use.

OTC - PREGNANCY OR BREAST FEEDING SECTION

If pregnant or breast-feeding, ask a doctor before use.

OTC - KEEP OUT OF REACH OF CHILDREN SECTION

Keep out of reach of children.